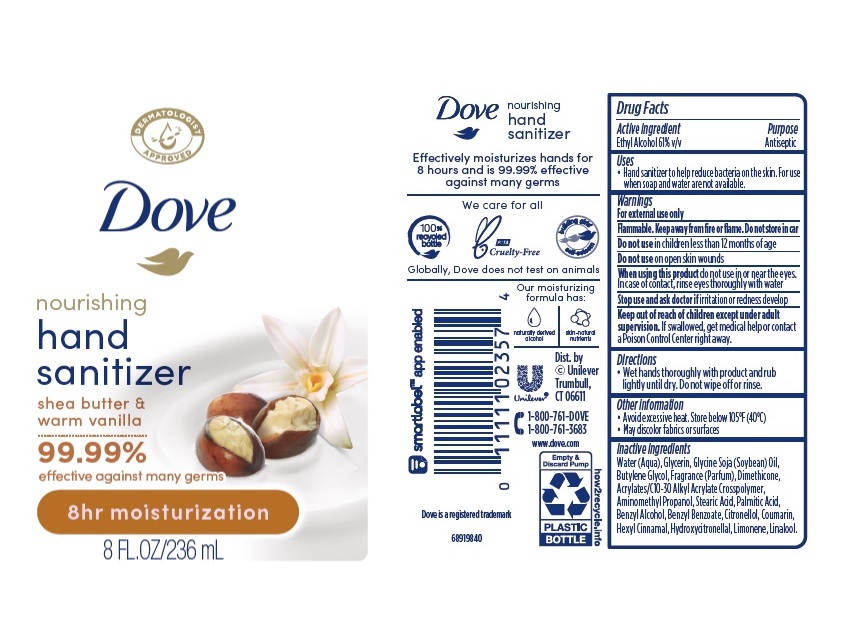 DRUG LABEL: Dove
NDC: 64942-2033 | Form: GEL
Manufacturer: Conopco Inc. d/b/a/ Unilever
Category: otc | Type: HUMAN OTC DRUG LABEL
Date: 20241107

ACTIVE INGREDIENTS: ALCOHOL 610 mg/1 mL
INACTIVE INGREDIENTS: STEARIC ACID; COUMARIN; PALMITIC ACID; BUTYLENE GLYCOL; WATER; GLYCERIN; LIMONENE, (+)-; DIMETHICONE; HYDROXYCITRONELLAL; BENZYL ALCOHOL; AMINOMETHYLPROPANOL; .BETA.-CITRONELLOL, (R)-; .ALPHA.-HEXYLCINNAMALDEHYDE; SOYBEAN OIL; LINALOOL, (+/-)-; BENZYL SALICYLATE

Dove Nourishing Hand Sanitizer Shea Butter & Warm Vanilla 8h Moisturization

DOVE NOURISHING HAND SANITIZER SHEA BUTTER & WARM VANILLA 8H MOISTURIZATION - Ethyl Alcohol gel

Dove Nourishing Hand Sanitizer Shea Butter & Warm Vanilla 8h Moisturization

Drug Facts

Active ingredient

Ethyl Alcohol 61%

Purpose

Antiseptic

Uses

• Hand sanitizer to help reduce bacteria on the skin. For use when soap and water are not available.

Warnings

For external use only
Flammable. Keep away from fire or flame
Do not use in children less than 12 months of age
Do not use on open skin wounds
When using this product, do not use in or near the eyes. In case of contact, rinse eyes thoroughly with water
Stop use and ask doctor if irritation or redness develop

• Keep out of reach of children except under adult supervision.

If swallowed, get medical help or contact a poison control Center right away.

Directions

• Wet hands thoroughly with product and rub lightly until dry. Do not wipe off or rinse.

Other information

• Store below 105˚F (40˚C).
• May discolor fabrics or surfaces.

Inactive ingredients

Water (Aqua), Glycerin, Glycine Soja (Soybean) Oil, Butylene Glycol, Fragrance (Parfum), Dimethicone, Acrylates/C10-30 Alkyl Acrylate Crosspolymer, Aminomethyl Propanol, Stearic Acid, Palmitic Acid, Benzyl Alcohol, Benzyl Salicylate, Citronellol, Coumarin, Hexyl Cinnamal, Hydroxycitronellal, Limonene, Linalool

Questions?

1-800-761-3683